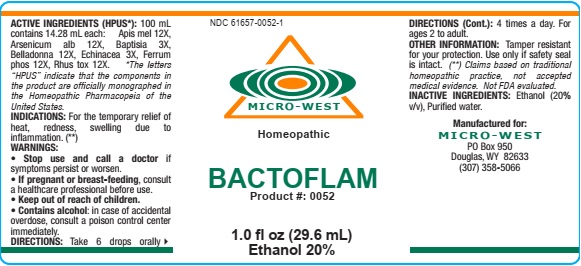 DRUG LABEL: BACTOFLAM
NDC: 61657-0052 | Form: LIQUID
Manufacturer: WHITE MANUFACTURING INC. DBA MICRO WEST
Category: homeopathic | Type: HUMAN OTC DRUG LABEL
Date: 20210121

ACTIVE INGREDIENTS: ECHINACEA, UNSPECIFIED 3 [hp_X]/30 mL; BAPTISIA TINCTORIA ROOT 3 [hp_X]/30 mL; APIS MELLIFERA 12 [hp_X]/30 mL; FERRUM PHOSPHORICUM 12 [hp_X]/30 mL; ATROPA BELLADONNA 12 [hp_X]/30 mL; TOXICODENDRON PUBESCENS LEAF 12 [hp_X]/30 mL; ARSENIC TRIOXIDE 12 [hp_X]/30 mL
INACTIVE INGREDIENTS: ALCOHOL

DRUG FACTS

ACTIVE INGREDIENTS

Apis mel 12X

Arsenicum alb 12X

Baptisia 3X

Belladonna 12X

Echinacea 3X

Ferrum phos 12X

Rhus tox 12X

INACTIVE INGREDIENT

Alcohol (20% v/v, Purified water

PURPOSE

TEMPORARY RELIEF OF HEAT, REDNESS, SWELLING DUE TO INFLAMMATION

KEEP OUT OF REACH OF CHILDREN

WARNINGS

WARNINGS: STOP USE AND CALL A DOCTOR IF symptoms persist or worsen. IF PREGNANT OR BREAST FEEDING, consult a healthcare professional before use. CONTAINS ALCOHOL: in case of accidental overdose, consult a poison control center immediately

INDICATIONS

FOR THE TEMPORARY RELIEF OF HEAT, REDNESS, SWELLING DUE TO INFLAMMATION

DIRECTIONS

Take 6 drops orally, 4 times a day. For ages 2 to adult.

MANUFACTURE

MANUFACTURED FOR MICRO WEST

DOUGLAS, WY 82633

1-307-358-5066

OTHER INFORMATION

Tamper resistant for you protection; use only if safety seal is intact

LABEL

NDC 61657-0052-1

MICRO-WEST

Homeopathic

BACTOFLAM

Product #: 0052

1.0 fl oz (29.6 mL)

Ethanol 20%